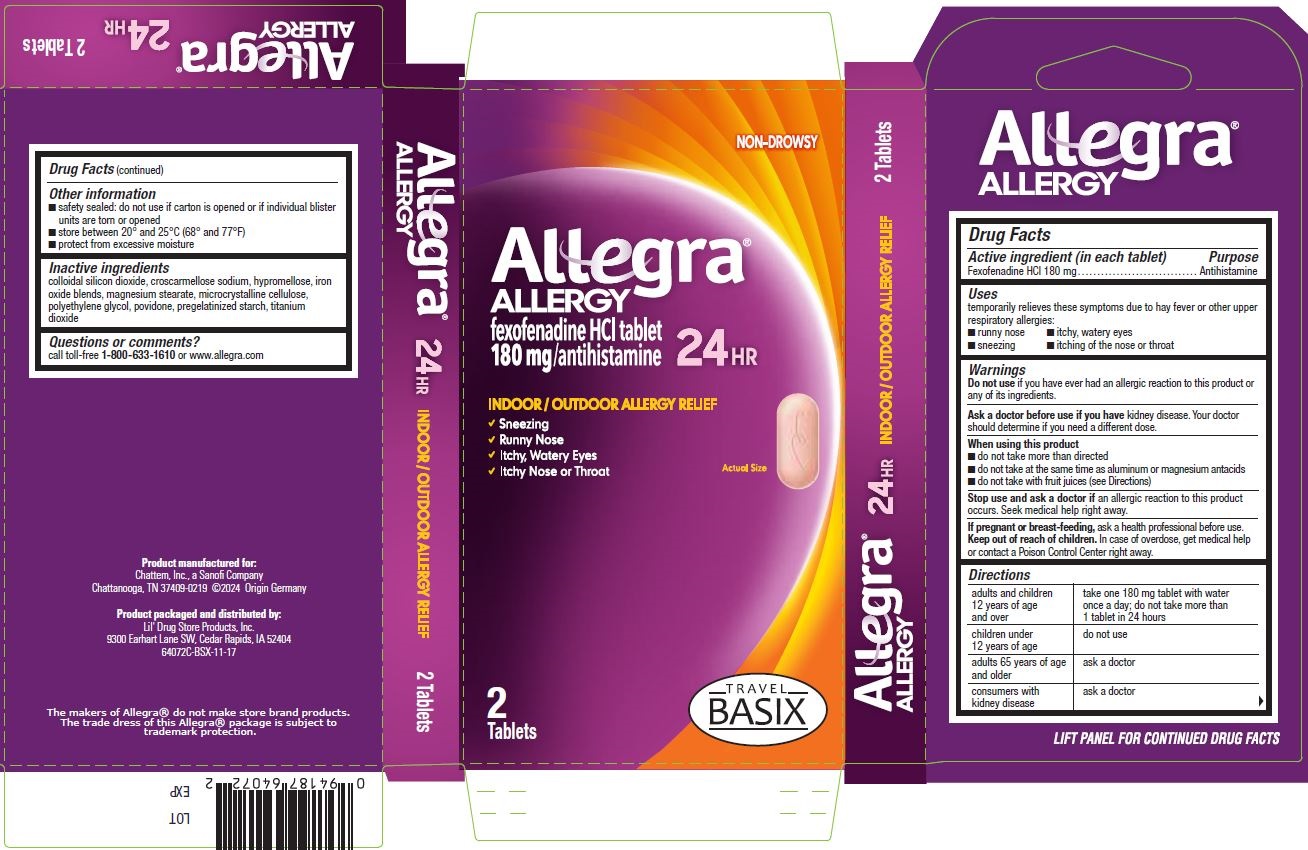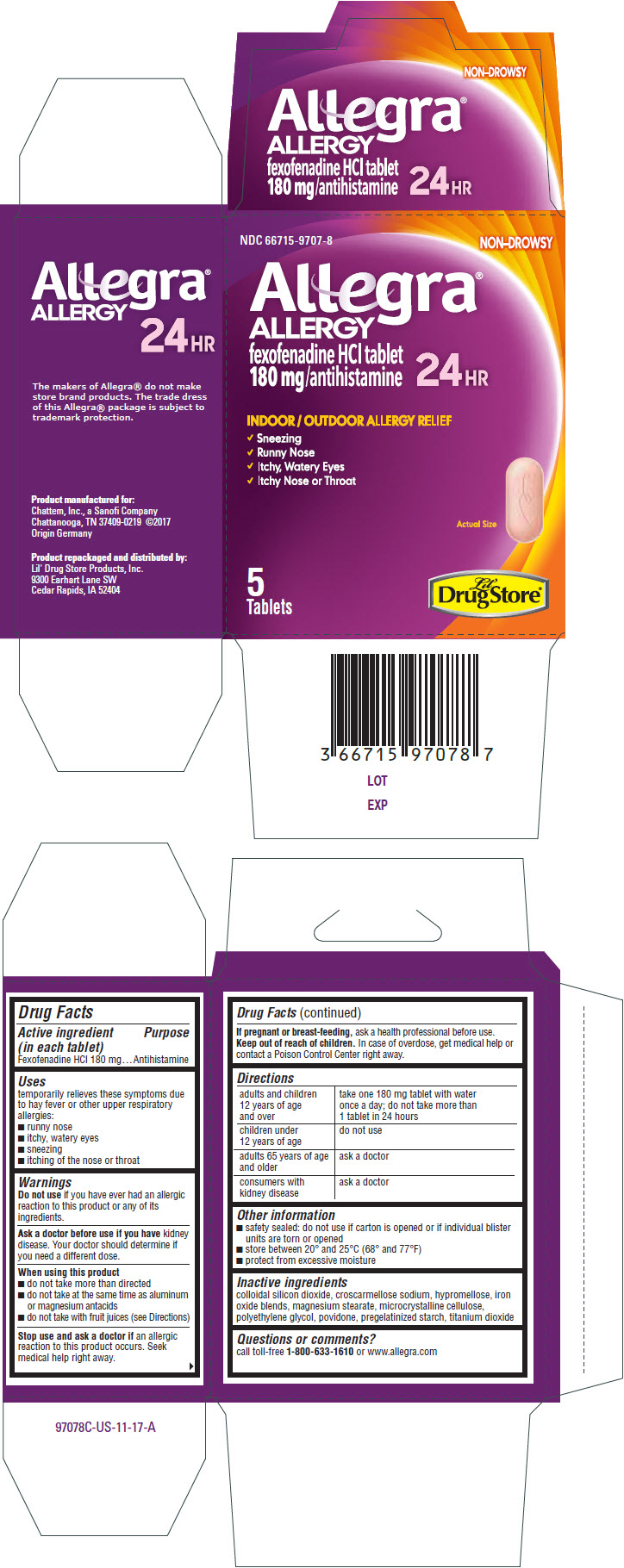 DRUG LABEL: Allegra Allergy
NDC: 66715-9707 | Form: TABLET, FILM COATED
Manufacturer: Lil' Drug Store Products, Inc
Category: otc | Type: HUMAN OTC DRUG LABEL
Date: 20241119

ACTIVE INGREDIENTS: FEXOFENADINE HYDROCHLORIDE 180 mg/1 1
INACTIVE INGREDIENTS: SILICON DIOXIDE; MICROCRYSTALLINE CELLULOSE; CROSCARMELLOSE SODIUM; HYPROMELLOSE, UNSPECIFIED; MAGNESIUM STEARATE; POLYETHYLENE GLYCOL, UNSPECIFIED; POVIDONE, UNSPECIFIED; STARCH, CORN; TITANIUM DIOXIDE

Allegra® Allergy

Drug Facts

Active ingredient (in each tablet)

Fexofenadine HCl 180 mg

Purpose

Antihistamine

Uses

temporarily relieves these symptoms due to hay fever or other upper respiratory allergies:

- runny nose
- itchy, watery eyes
- sneezing
- itching of the nose or throat

Warnings

Do not use if you have ever had an allergic reaction to this product or any of its ingredients.

Ask a doctor before use if you have kidney disease. Your doctor should determine if you need a different dose.

When using this product

- do not take more than directed
- do not take at the same time as aluminum or magnesium antacids
- do not take with fruit juices (see Directions)

Stop use and ask a doctor if an allergic reaction to this product occurs. Seek medical help right away.

PREGNANCY OR BREAST FEEDING

If pregnant or breast-feeding, ask a health professional before use.

Keep out of reach of children. In case of overdose, get medical help or contact a Poison Control Center right away.

Directions

adults and children 12 years of age and over | take one 180 mg tablet with water once a day; do not take more than 1 tablet in 24 hours
children under 12 years of age | do not use
adults 65 years of age and older | ask a doctor
consumers with kidney disease | ask a doctor

Other information

- safety sealed: do not use if carton is opened or if individual blister units are torn or opened
- store between 20° and 25°C (68° and 77°F)
- protect from excessive moisture

Inactive ingredients

colloidal silicon dioxide, croscarmellose sodium, hypromellose, iron oxide blends, magnesium stearate, microcrystalline cellulose, polyethylene glycol, povidone, pregelatinized starch, titanium dioxide

Questions or comments?

call toll-free 1-800-633-1610 or www.allegra.com

Product repackaged and distributed by:
Lil' Drug Store Products, Inc.
9300 Earhart Lane SW
Cedar Rapids, IA 52404

PRINCIPAL DISPLAY PANEL - 5 Tablet Blister Pack Carton

NDC 66715-9707-8
NON-DROWSY

Allegra®
ALLERGY
fexofenadine HCl tablet
180 mg/antihistamine
24 HR

INDOOR / OUTDOOR ALLERGY RELIEF

✓ Sneezing
✓ Runny Nose
✓ Itchy, Watery Eyes
✓ Itchy Nose or Throat

Actual Size

5
Tablets

Lil'
DrugStore®

Allegra Allergy, Travel BASIX

NON-DROWSY

Allegra®
ALLERGY
fexofenadine HCl tablet
180 mg/antihistamine
24 HR

INDOOR / OUTDOOR ALLERGY RELIEF

✓ Sneezing
✓ Runny Nose
✓ Itchy, Watery Eyes
✓ Itchy Nose or Throat

Actual Size [tablet image]

2
Tablets

[TRAVEL BASIX logo]